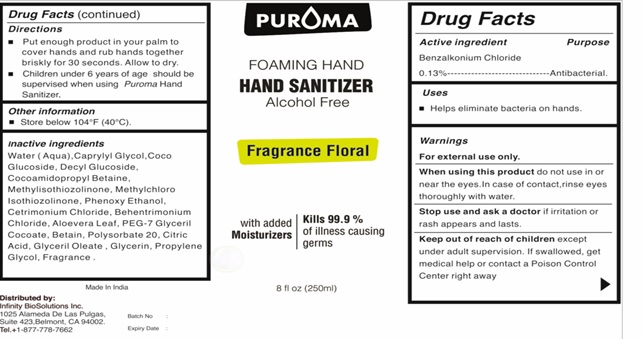 DRUG LABEL: PUROMA  Foaming Hand Sanitizer Alcohol Free  With Fragrance Floral
NDC: 80948-016 | Form: LIQUID
Manufacturer: ZENITH MICRO CONTROL
Category: otc | Type: HUMAN OTC DRUG LABEL
Date: 20231214

ACTIVE INGREDIENTS: BENZALKONIUM CHLORIDE 130 mg/100 mL
INACTIVE INGREDIENTS: WATER; METHYLCHLOROISOTHIAZOLINONE; GLYCERIN; METHYLISOTHIAZOLINONE; CETRIMONIUM CHLORIDE; CAPRYLYL GLYCOL; PROPYLENE GLYCOL; CITRIC ACID MONOHYDRATE; PHENOXYETHANOL; DECYL GLUCOSIDE; COCO GLUCOSIDE; GLYCERYL OLEATE; COCAMIDOPROPYL BETAINE; BEHENTRIMONIUM CHLORIDE; PEG-7 GLYCERYL COCOATE; FRAGRANCE FLORAL ORC0902236; BETAINE; ALOE VERA LEAF; POLYSORBATE 20

Active ingredient

Benzalkonium chloride 0.13%

Purpose

Antibacterial

Uses

Helps eliminate bacteria on hands.

Warnings

For external use only.
When using this product do not use in or near the eyes. In case of contact, rinse eyes thoroughly with water.
Stop use and ask a doctor if irritation or rash appears and lasts.

Keep out of reach of children

except under adult supervision. If swallowed, get medical help or contact a Poison Control Center right away.

Directions

• Put enough product in your palm to cover hands and rub hands together briskly for 30 seconds. Allow to dry.
• Children under 6 years of age should be supervised when using Puroma Hand Sanitizer.

Other information

Store below 104°F (40°C)

Inactive ingredient

Water (Aqua), Caprylyl Glycol, Coco Glucoside, Decyl Glucoside, Cocoamidopropyl Betaine, Methylisothiozolinone, Methylchloro Isothiozolinone, Phenoxy Ethanol, Cetrimonium Chloride, Behentrimonium Chloride, Aloevera Leaf, PEG-7 Glyceril Cocoate, Betain, Polysorbate 20, Citric Acid, Glyceril Oleate , Glycerin, Propylene Glycol, Fragrance Floral ORC0902236.